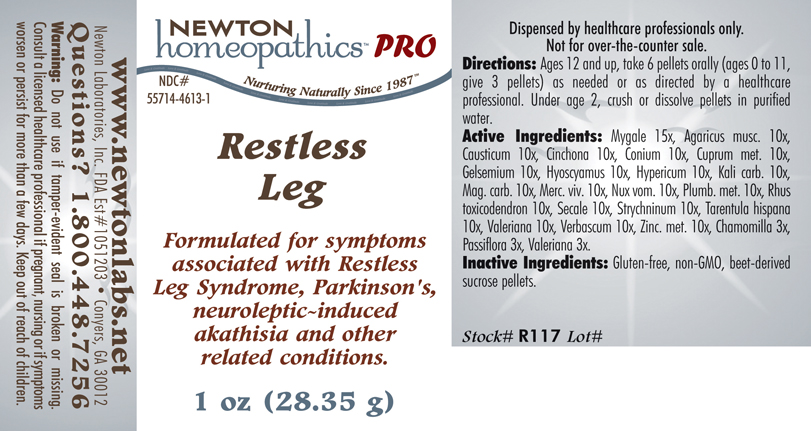 DRUG LABEL: Restless Leg 
NDC: 55714-4613 | Form: PELLET
Manufacturer: Newton Laboratories, Inc.
Category: homeopathic | Type: HUMAN PRESCRIPTION DRUG LABEL
Date: 20110601

ACTIVE INGREDIENTS: Avicularia Avicularia 15 [hp_X]/1 g; Amanita Muscaria Var. Muscaria Fruiting Body 10 [hp_X]/1 g; Causticum 10 [hp_X]/1 g; Cinchona Officinalis Bark 10 [hp_X]/1 g; Conium Maculatum Flowering Top 10 [hp_X]/1 g; Copper 10 [hp_X]/1 g; Gelsemium Sempervirens Root 10 [hp_X]/1 g; Hyoscyamus Niger 10 [hp_X]/1 g; Hypericum Perforatum 10 [hp_X]/1 g; Potassium Carbonate 10 [hp_X]/1 g; Magnesium Carbonate 10 [hp_X]/1 g; Mercury 10 [hp_X]/1 g; Strychnos Nux-vomica Seed 10 [hp_X]/1 g; Lead 10 [hp_X]/1 g; Toxicodendron Pubescens Leaf 10 [hp_X]/1 g; Claviceps Purpurea Sclerotium 10 [hp_X]/1 g; Strychnine 10 [hp_X]/1 g; Lycosa Tarantula 10 [hp_X]/1 g; Valerian 10 [hp_X]/1 g; Verbascum Thapsus 10 [hp_X]/1 g; Zinc 10 [hp_X]/1 g; Matricaria Recutita 3 [hp_X]/1 g; Passiflora Incarnata Flowering Top 3 [hp_X]/1 g
INACTIVE INGREDIENTS: Sucrose

Restless Leg

INDICATIONS & USAGE SECTION

Restless Leg Formulated for symptoms associated with Restless Leg Syndrome, Parkinson's, neuroleptic~induced akathisia and other related conditions.

DOSAGE & ADMINISTRATION SECTION

Directions: Ages 12 and up, take 6 pellets orally (ages 0 to 11, give 3 pellets) as needed or as directed by a healthcare professional. Under age 2, crush or dissolve pellets in purified water.

ACTIVE INGREDIENT SECTION

Mygale 15x, Agaricus musc. 10x, Causticum 10x, Cinchona 10x, Conium 10x, Cuprum met. 10x, Gelsemium 10x, Hyoscyamus 10x, Hypericum 10x, Kali carb. 10x ,Mag. carb. 10x, Merc. viv. 10x, Nux vom. 10x, Plumb. met. 10x, Rhus toxicodendron 10x, Secale 10x, Strychninum 10x, Tarentula hispana 10x, Valeriana 10x, Verbascum 10x, Zinc. met. 10x, Chamomilla 3x, Passiflora 3x, Valeriana 3x.

PURPOSE SECTION

Formulated for symptoms associated with Restless Leg Syndrome, Parkinson's, neuroleptic-induced akathisia and other related conditions.

INACTIVE INGREDIENT SECTION

Inactive Ingredients: Gluten-free, non-GMO, beet-derived sucrose pellets.

QUESTIONS? SECTION

www.newtonlabs.net Newton Laboratories, Inc. FDA Est # 1051203 - Conyers, GA 30012
Questions? 1.800.448.7256

WARNINGS SECTION

Warning: Do not use if tamper - evident seal is broken or missing. Consult a licensed healthcare professional if pregnant, nursing or if symptoms worsen or persist for more than a few days. Keep out of reach of children.

PREGNANCY OR BREAST FEEDING SECTION

Consult a licensed healthcare professional if pregnant, nursing or if symptoms worsen or persist for more than a few days.

KEEP OUT OF REACH OF CHILDREN SECTION

Keep out of reach of children